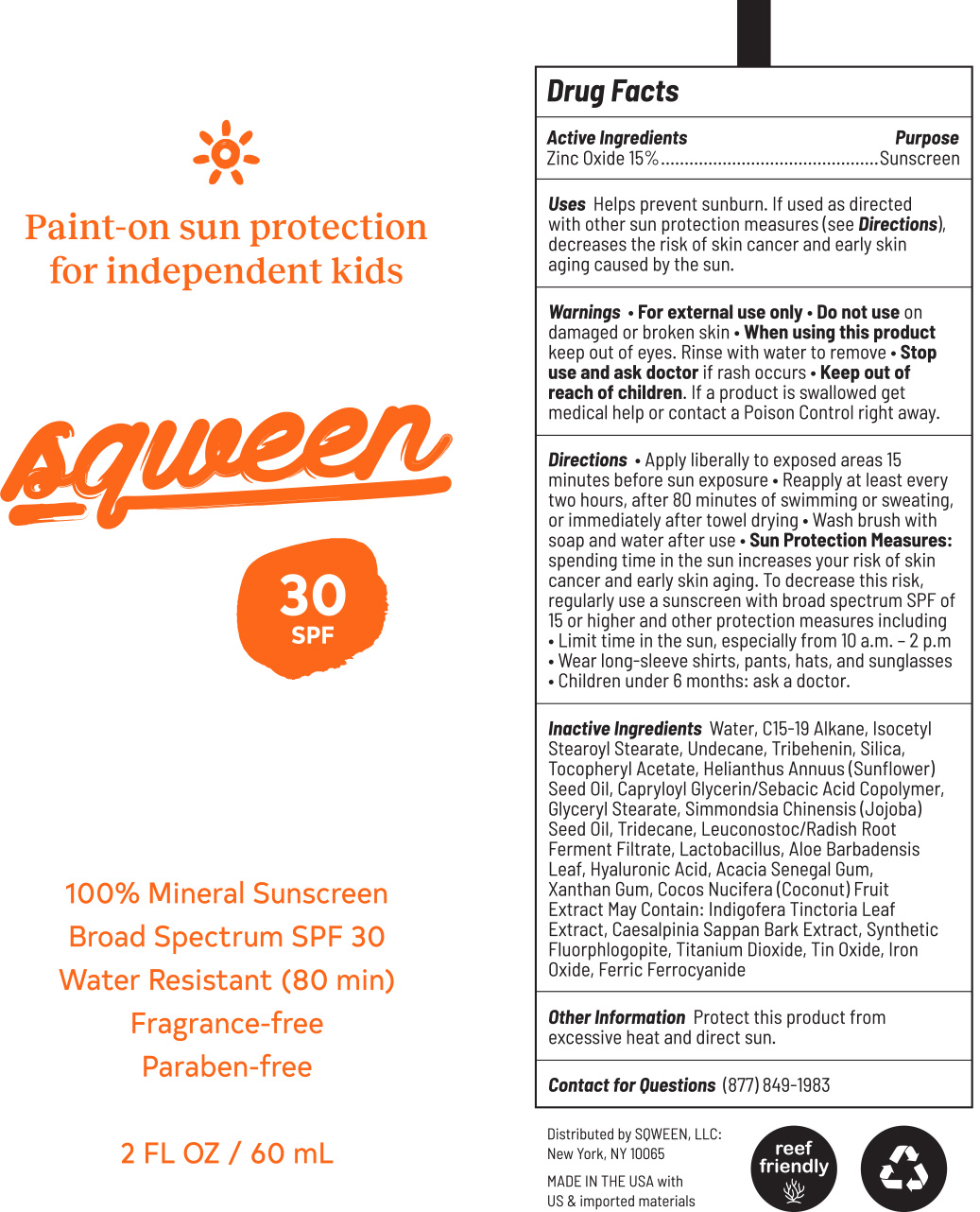 DRUG LABEL: Sqween 100% Mineral Sunscreen Broad Spectrum SPF 30 Water Resistant
NDC: 83005-0001 | Form: LOTION
Manufacturer: SQWEEN LLC
Category: otc | Type: HUMAN OTC DRUG LABEL
Date: 20240624

ACTIVE INGREDIENTS: ZINC OXIDE 150 mg/1 mL
INACTIVE INGREDIENTS: WATER; C15-19 ALKANE; ISOCETYL STEAROYL STEARATE; UNDECANE; TRIBEHENIN; SILICON DIOXIDE; .ALPHA.-TOCOPHEROL ACETATE; SUNFLOWER OIL; CAPRYLOYL GLYCERIN/SEBACIC ACID COPOLYMER (2000 MPA.S); GLYCERYL MONOSTEARATE; JOJOBA OIL; TRIDECANE; LEUCONOSTOC/RADISH ROOT FERMENT FILTRATE; ALOE VERA LEAF; HYALURONIC ACID; ACACIA; XANTHAN GUM; COCONUT; INDIGOFERA TINCTORIA LEAF; BIANCAEA SAPPAN BARK; MAGNESIUM POTASSIUM ALUMINOSILICATE FLUORIDE; TITANIUM DIOXIDE; STANNIC OXIDE

Sqween 100% Mineral Sunscreen Broad Spectrum SPF 30 Water Resistant

Active Ingredients

Zinc Oxide 15%

Purpose

Sunscreen

Uses

Helps prevent surnburn. If used as directed with other sun protection measures (See), decreases the risk of skin cancer and early skin aging caused by the skin. Directions

Warning

For external use only

Do not use

on damaged or broken skin

When using this product

Keep out of eyes. Rinse with water to remove.

Stop use and ask doctor

if rash occurs.

Keep out of reach of children.

If a product is swallowed get medical help or contact a Poison Control right away.

Directions

Apply liberally to exposed areas 15 minutes before sun exposure.

Reapply at least every two hours, after 80 minutes of swimming or sweating, or immediately after towel drying.

- Spending time in the sun increases your risk of skin cancer and early skin aging. To decrease the risk, regularly use a sunscreen with broad spectrum SPF of 15 or higher and other protection measures including Sun Protection Measures
- Limit time in the sun, especially from 10 a.m. - 2 p.m.
- Wear long-sleeve shirts, pants, hats, and sunglasses
- Children under 6 months: ask a doctor.

INACTIVE INGREDIENT

Inactive Ingredients: Water, C15-19 Alkane, Isocetyl Stearoyl Stearate, Undecane, Tribehenin, Silica, Tocopheryl Acetate, Helianthus Annuus (Sunflower) Seed Oil, Capryloyl Glycerin/Sebacic Acid Copolymer, Glyceryl Stearate, Simmondsia Chinensis (Jojoba) Seed Oil, Tridecane, Leuconostoc/Radish Root Ferment Filtrate, Lactobacillus, Aloe Barbadensis Leaf, Hyaluronic Acid, Acacia Senegal Gum, Xanthan Gum, Cocos Nucifera (Coconut) Fruit Extract May Contain: Indigofera Tinctoria Leaf Extract, Caesalpinia Sappan Bark Extract, Synthetic Fluorphlogopite, Titanium Dioxide, Tin Oxide

Other Information

Protect this product from excessive heat and direct sun.

Contact for Questions: (877) 849-1983

Distributed by SQWEEN, LLC: New York, NY 10065

MADE IN THE USA with US & imported materials